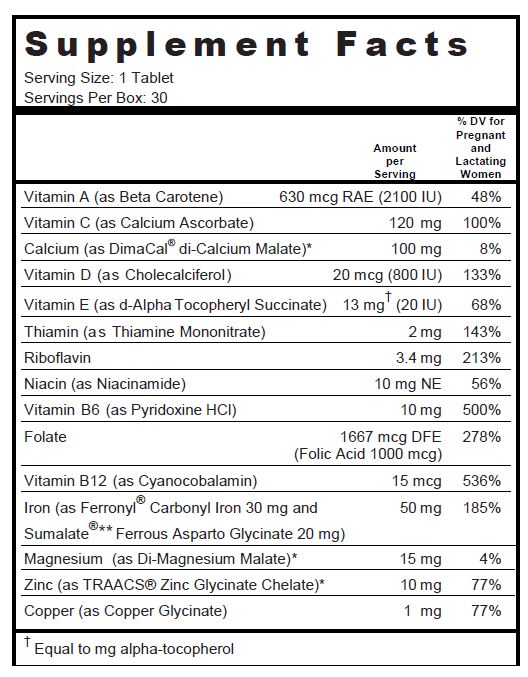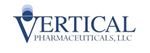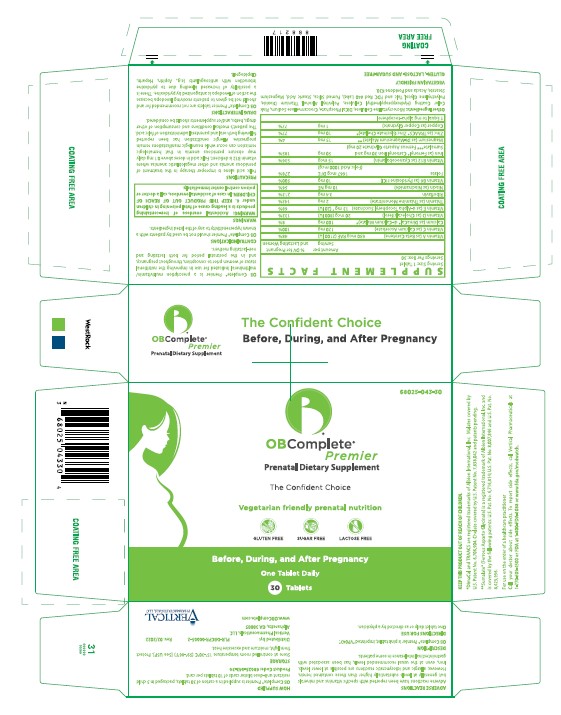 DRUG LABEL: OB Complete Premier
NDC: 68025-043 | Form: TABLET, COATED
Manufacturer: Vertical Pharmaceuticals, LLC
Category: other | Type: DIETARY SUPPLEMENT
Date: 20220218

ACTIVE INGREDIENTS: BETA CAROTENE 2100 [iU]/1 1; CALCIUM ASCORBATE 120 mg/1 1; CHOLECALCIFEROL 800 [iU]/1 1; .ALPHA.-TOCOPHEROL SUCCINATE, D- 20 [iU]/1 1; THIAMINE MONONITRATE 2 mg/1 1; RIBOFLAVIN 3.4 mg/1 1; NIACINAMIDE 10 mg/1 1; PYRIDOXINE HYDROCHLORIDE 10 mg/1 1; FOLIC ACID 1 mg/1 1; CYANOCOBALAMIN 15 ug/1 1; CALCIUM MALATE 100 mg/1 1; IRON PENTACARBONYL 30 mg/1 1; FERROUS ASPARTO GLYCINATE 20 mg/1 1; MAGNESIUM MALATE 15 mg/1 1; ZINC GLYCINATE 10 mg/1 1; CUPRIC GLYCINATE 1 mg/1 1
INACTIVE INGREDIENTS: CELLULOSE, MICROCRYSTALLINE; CALCIUM PHOSPHATE; CROSCARMELLOSE SODIUM; HYPROMELLOSES; POLYVINYL ALCOHOL, UNSPECIFIED; TITANIUM DIOXIDE; POLYETHYLENE GLYCOL, UNSPECIFIED; TALC; FD&C RED NO. 40; SILICON DIOXIDE; STEARIC ACID; MAGNESIUM STEARATE; ACACIA; POVIDONE K30

OB Complete® Premier

SUPPLEMENT FACTS

Other Ingredients: Microcrystalline Cellulose, DiCal Phosphate, Croscarmellose Sodium, Pink Color Coating (Hydroxypropylmethyl Cellulose, Polyvinyl Alcohol, Titanium Dioxide, Polyethylene Glycol, Talc and FDC Red #40 Lake), Fumed Silica, Stearic Acid, Magnesium Stearate, Acacia and Povidone K30.

VEGETARIAN FRIENDLY

GLUTEN-, LACTOSE- AND SUGAR-FREE

OB Complete® Premier is a prescription multivitamin/multimineral indicated for use in improving the nutritional status of women prior to conception, throughout pregnancy, and in the postnatal period for both lactating and non-lactating mothers.

CONTRAINDICATIONS

OB Complete® Premier should not be used by patients with a known hypersensitivity to any of the listed ingredients.

WARNINGS

WARNING: Accidental overdose of iron-containing products is a leading cause of fatal poisoning in children under 6. KEEP OUT OF REACH OF CHILDREN. In case of accidental overdose, call a doctor or poison control center immediately.

PRECAUTIONS

Folic acid alone is improper therapy in the treatment of pernicious anemia and other megaloblastic anemias where vitamin B12 is deficient. Folic acid in doses above 0.1 mg daily may obscure pernicious anemia in that hematologic remission can occur while neurologic manifestations remain progressive. Allergic sensitization has been reported following both oral and parenteral administration of folic acid.

The patient’s medical conditions and consumption of other drugs, herbs, and/or supplements should be considered.

DRUG INTERACTIONS

OB Complete® Premier tablets are not recommended for and should not be given to patients receiving levodopa because the action of levodopa is antagonized by pyridoxine. There is a possibility of increased bleeding due to pyridoxine interaction with anticoagulants (e.g., Aspirin, Heparin, Clopidogrel).

ADVERSE REACTIONS

Adverse reactions have been reported with specific vitamins and minerals but generally at levels substantially higher than those contained herein. However, allergic and idiosyncratic reactions are possible at lower levels. Iron, even at the usual recommended levels, has been associated with gastrointestinal intolerance in some patients.

DESCRIPTION

OB Complete® Premier is pink tablet, imprinted "VP043".

DIRECTIONS FOR USE

One tablet daily or as directed by a physician.

HOW SUPPLIED

OB Complete® Premier is supplied in a carton of 30 tablets, packaged in 3 child resistant unit-dose blister cards of 10 tablets per card.

Product Code: 68025-043-30

STORAGE

Store at controlled room temperature 15°-30°C (59°-86°F) [See USP]. Protect from light, moisture and excessive heat.

HEALTH CLAIM

KEEP THIS PRODUCT OUT OF REACH OF CHILDREN.

*DimaCal and TRAACS are registered trademarks of Albion International, Inc. Malates covered by U.S. Patent No. 6,706,904. Chelate covered by U.S. Patent No. 7,838,042 and patents pending.

**Sumalate® (Ferrous Asparto Glycinate) is a registered trademark of Albion International, Inc. and is covered by the following patents: U.S. Pat. No. 6,716,814; U.S. Pat. No. 8,007,846 and U.S. Pat. No. 8,425,956.

For use on the order of a healthcare practitioner

Call your doctor about side effects. To report side effects, call Vertical Pharmaceuticals at 1-770-509-4500 or FDA at 1-800-FDA-1088 or www.fda.gov/medwatch.

PLR-OBCPR-00005-2 Rev. 02/2022

Distributed by:
Vertical Pharmaceuticals, LLC
Alpharetta, GA 30005

PRINCIPAL DISPLAY PANEL - 30 Tablet Blister Pack Carton

68025-043-30

Vegetarian Friendly,
Gluten, Lactose and
Sugar-Free

OB
COMPLETE®
Premier

30 Tablets

VERTICAL
PHARMACEUTICALS, LLC